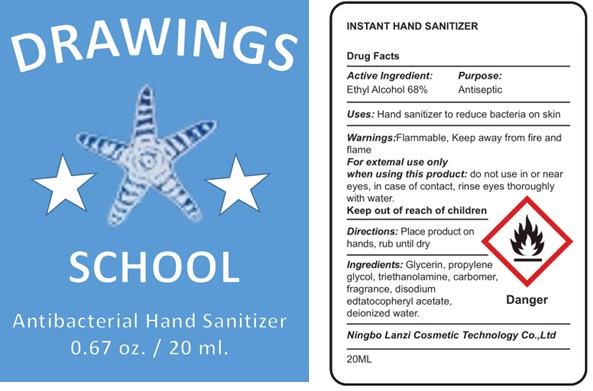 DRUG LABEL: Instant hand sanitizer
NDC: 80575-003 | Form: SPRAY
Manufacturer: National Design LLC
Category: otc | Type: HUMAN OTC DRUG LABEL
Date: 20200929

ACTIVE INGREDIENTS: ALCOHOL 0.68 mL/1 mL
INACTIVE INGREDIENTS: GLYCERIN; PROPYLENE GLYCOL; TROLAMINE; CARBOMER HOMOPOLYMER, UNSPECIFIED TYPE; EDETATE DISODIUM ANHYDROUS; .ALPHA.-TOCOPHEROL ACETATE; WATER

Instant hand sanitizer

Active ingredient:

Ethyl Alcohol 68%

Purpose:

Antiseptic

Uses:

- Hand sanitizer reduce bacteria on skin

Warnings:

Flammable, Keep away from fire and flame.

For external use only

When using this product:

do not use in or near eyes, in case of contact, rinse eyes thoroughly with water.

Directions:

Place product on hands, rub untill dry

Ingreidients:

Glycerin, propylene glycol, triethanolamine, carbomer, fragrance, disodium edta,tocopheryl acetate, deionized water.